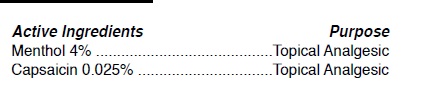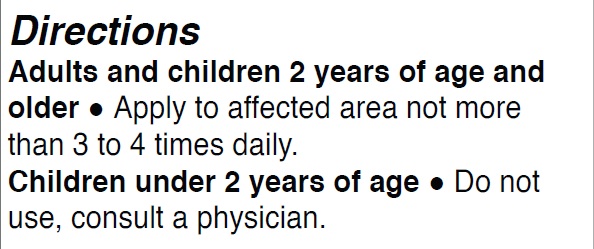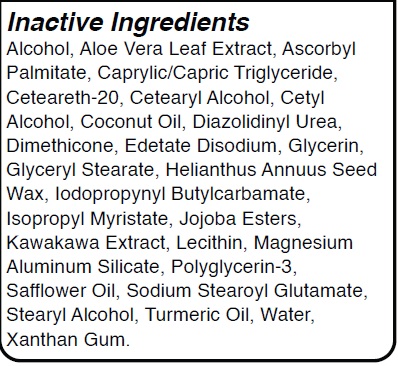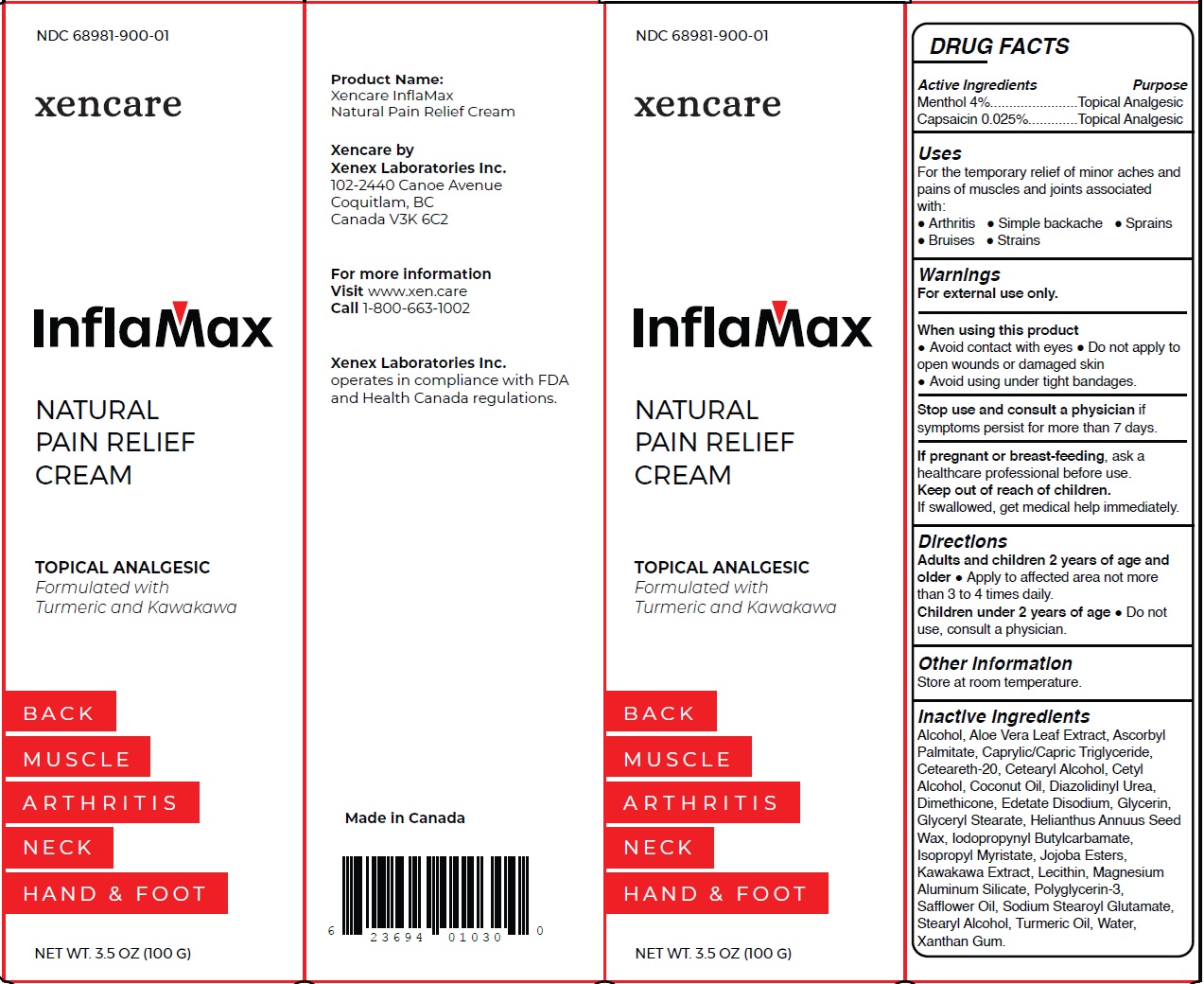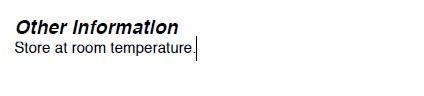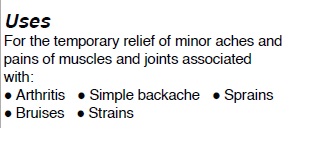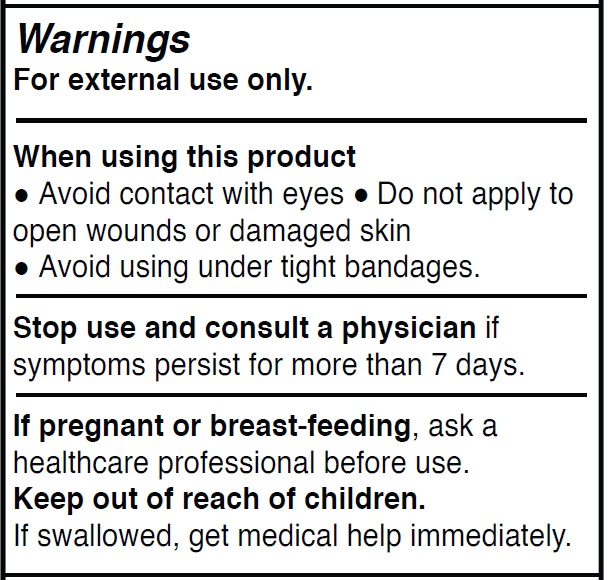 DRUG LABEL: XENCARE INFLAMAX NATURAL TOPICAL PAIN
NDC: 68981-900 | Form: CREAM
Manufacturer: Xenex Laboratories Inc.
Category: otc | Type: HUMAN OTC DRUG LABEL
Date: 20250306

ACTIVE INGREDIENTS: CAPSAICIN 0.025 g/100 g; LEVOMENTHOL 4 g/100 g
INACTIVE INGREDIENTS: CAPRYLIC/CAPRIC TRIGLYCERIDE; EDETATE DISODIUM; KAWAKAWA; JOJOBA OIL; GLYCERYL STEARATE; HELIANTHUS ANNUUS SEED WAX; CETEARETH-20; LECITHIN, SOYBEAN; COCONUT OIL; CETEARYL ALCOHOL; IODOPROPYNYL BUTYLCARBAMATE; SODIUM STEAROYL GLUTAMATE; XANTHAN GUM; DIMETHICONE; GLYCERIN; CETYL ALCOHOL; WATER; STEARYL ALCOHOL; ISOPROPYL MYRISTATE; TURMERIC OIL; ALOE VERA LEAF; MAGNESIUM ALUMINUM SILICATE; POLYGLYCERIN-3; ALCOHOL; SAFFLOWER OIL; ASCORBYL PALMITATE; DIAZOLIDINYL UREA

Active Ingredients Purpose
Menthol 4% .................................................Topical Analgesic
Capsaicin 0.025% .........................................Topical Analgesic

Uses
For the temporary relief of minor aches and
pains of muscles and joints associated
with:
• Arthritis • Simple backache • Sprains
• Bruises • Strains

Directions
Adults and children 2 years of age and
older • Apply to affected area not more
than 3 to 4 times daily.
Children under 2 years of age • Do not
use, consult a physician.

Other Information

Store at room temperature.

Inactive Ingredients
Alcohol, Aloe Vera Leaf Extract, Ascorbyl
Palmitate, Caprylic/Capric Triglyceride,
Ceteareth-20, Cetearyl Alcohol, Cetyl
Alcohol, Coconut Oil, Diazolidinyl Urea,
Dimethicone, Edetate Disodium, Glycerin,
Glyceryl Stearate, Helianthus Annuus Seed
Wax, Iodopropynyl Butylcarbamate,
Isopropyl Myristate, Jojoba Esters,
Kawakawa Extract, Lecithin, Magnesium
Aluminum Silicate, Polyglycerin-3,
Safflower Oil, Sodium Stearoyl Glutamate,
Stearyl Alcohol, Turmeric Oil, Water,
Xanthan Gum.

Warnings
For external use only.

When using this product
• Avoid contact with eyes • Do not apply to
open wounds or damaged skin
• Avoid using under tight bandages.

Stop use and consult a physician if
symptoms persist for more than 7 days.

If pregnant or breast-feeding, ask a
healthcare professional before use.
Keep out of reach of children.
If swallowed, get medical help immediately.

Warnings
For external use only.

When using this product
• Avoid contact with eyes • Do not apply to
open wounds or damaged skin
• Avoid using under tight bandages.

Stop use and consult a physician if
symptoms persist for more than 7 days.

If pregnant or breast-feeding, ask a
healthcare professional before use.
Keep out of reach of children.
If swallowed, get medical help immediately.

Warnings
For external use only.

When using this product
• Avoid contact with eyes • Do not apply to
open wounds or damaged skin
• Avoid using under tight bandages.

Stop use and consult a physician if
symptoms persist for more than 7 days.

If pregnant or breast-feeding, ask a
healthcare professional before use.
Keep out of reach of children.
If swallowed, get medical help immediately.

Warnings
For external use only.

When using this product
• Avoid contact with eyes • Do not apply to
open wounds or damaged skin
• Avoid using under tight bandages.

Stop use and consult a physician if
symptoms persist for more than 7 days.

If pregnant or breast-feeding, ask a
healthcare professional before use.
Keep out of reach of children.
If swallowed, get medical help immediately.

Warnings
For external use only.

When using this product
• Avoid contact with eyes • Do not apply to
open wounds or damaged skin
• Avoid using under tight bandages.

Stop use and consult a physician if
symptoms persist for more than 7 days.

If pregnant or breast-feeding, ask a
healthcare professional before use.
Keep out of reach of children.
If swallowed, get medical help immediately.

Uses
For the temporary relief of minor aches and
pains of muscles and joints associated
with:
• Arthritis • Simple backache • Sprains
• Bruises • Strains

Warnings
For external use only.

When using this product
• Avoid contact with eyes • Do not apply to
open wounds or damaged skin
• Avoid using under tight bandages.

Stop use and consult a physician if
symptoms persist for more than 7 days.

If pregnant or breast-feeding, ask a
healthcare professional before use.
Keep out of reach of children.
If swallowed, get medical help immediately.

Change to Indications and Usage, Directions sections

Formatting of the following sections were changed:

- Indications and Usage
- Dosage and Administration

Contents remain the same as before.

March 2025